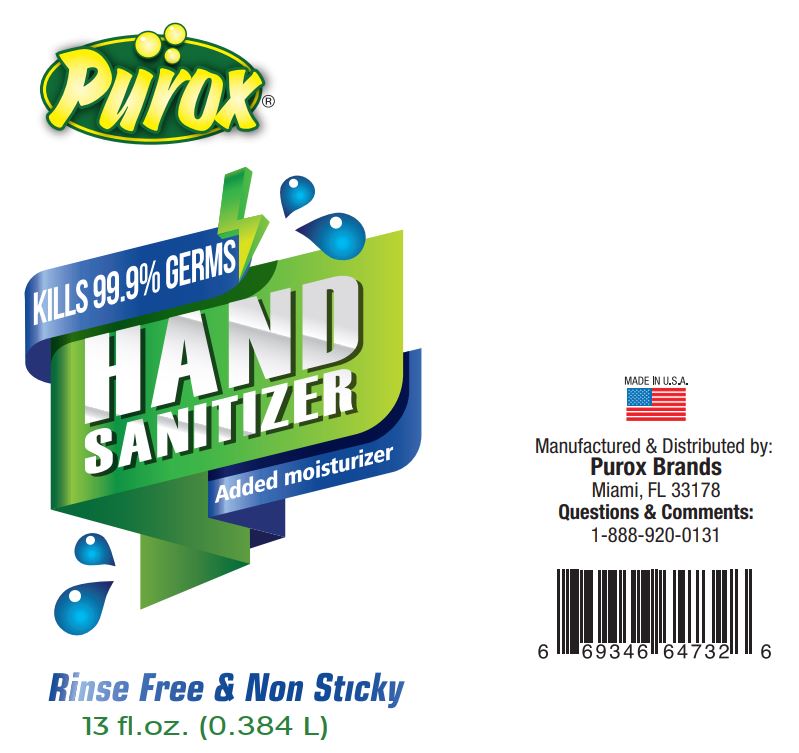 DRUG LABEL: Purox Hand Sanitizer
NDC: 78186-001 | Form: GEL
Manufacturer: Purox
Category: otc | Type: HUMAN OTC DRUG LABEL
Date: 20201222

ACTIVE INGREDIENTS: ALCOHOL 85 L/100 L
INACTIVE INGREDIENTS: ALOE 0.05 L/100 L; TROLAMINE 0.03 L/100 L; POLYACRYLIC ACID (250000 MW) 1.45 L/100 L; WATER 13.47 L/100 L

Active Ingredient

Alcohol 85% v/v

Purpose

Antimicrobial

Use

Hand Sanitizer to help reduce bacteria on the skin.

Warnings

Flammable. Keep away from heat or flame

For external use only

When using this product

- do not use in or near the eyes. In case of contact, rinse eyes thoroughly with water.

Stop use and ask a doctor if

- irritation or rash appears and lasts.

Keep out of reach of children. If swallowed, get medical help or contact a Poison Control Center right away.

Do not use

- in children less than 2 months of age
- on open skin wounds

Directions

- Place enough product in your palm to thoroughly spread on both hands and rub into th skin until dry.
- Children under 6 years old should be supervised when using this product.

Other information:

- store between 106F (41C)
- may discolor certain fabrics or surfaces

Inactive ingredients:

Deionized Water, Aloe, Triethanolamine, Carbomer